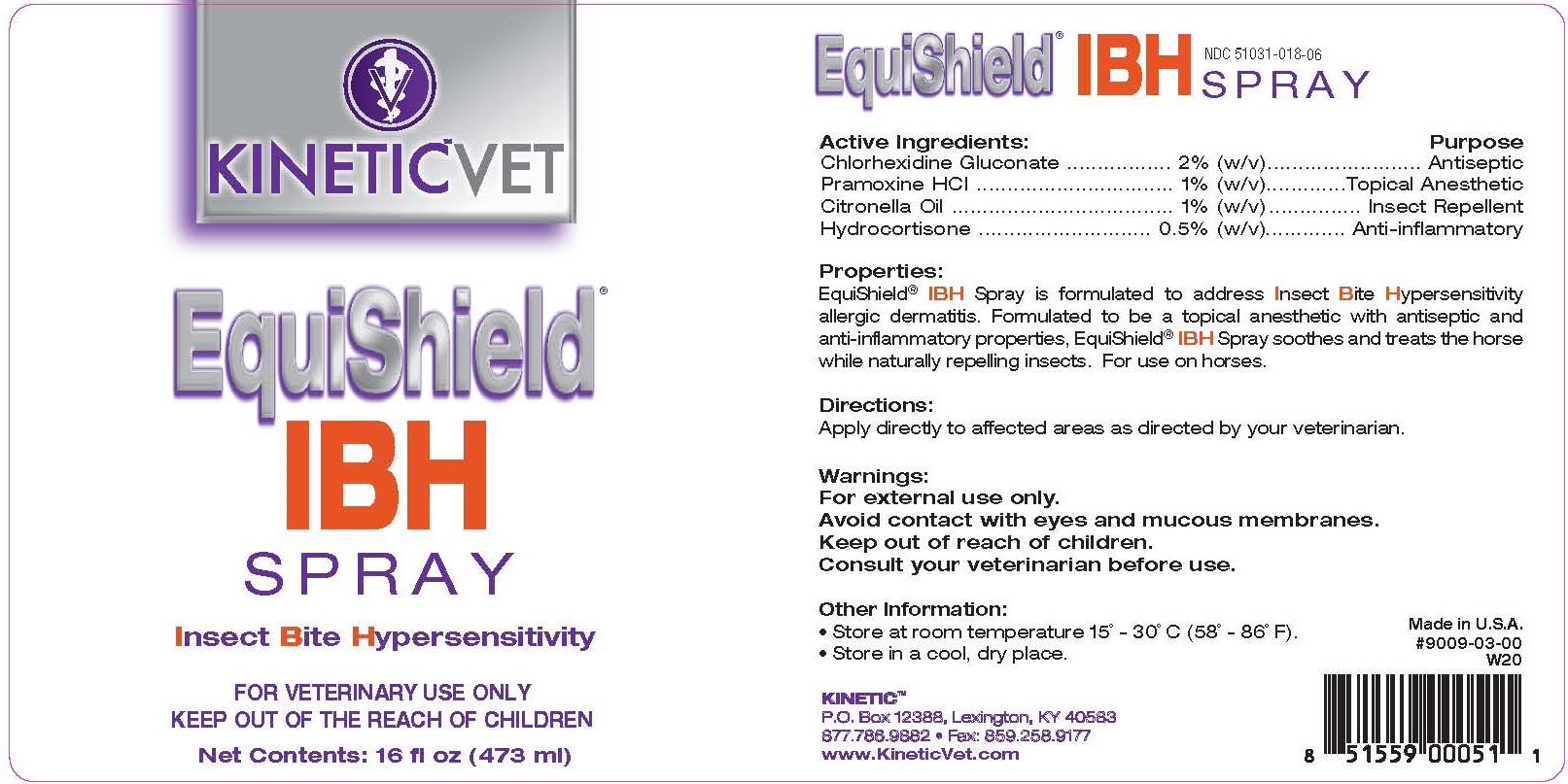 DRUG LABEL: EquiShield IBH
NDC: 51031-018 | Form: SPRAY
Manufacturer: Kinetic Technologies, LLC
Category: animal | Type: OTC ANIMAL DRUG LABEL
Date: 20231127

ACTIVE INGREDIENTS: CHLORHEXIDINE GLUCONATE 2 g/100 mL; PRAMOXINE HYDROCHLORIDE 1 g/100 mL; CITRONELLA OIL 1 g/100 mL; HYDROCORTISONE 0.5 g/100 mL

EquiShield IBH Spray

Active Ingredients:

Chlorhexidine Gluconate ........... 2% (w/v)...................... Antiseptic

Pramoxine HCL ........................ 1% (w/v)........... Topical Anesthetic

Citronella Oil ........................... 1% (w/v).............. Insect Repellant

Hydrocortisone ..................... 0.5% (w/v)........... Anti-inflammatory

Properties:

EquiShield® IBH Spray is formulated to address Insect Bite Hypersensitivity allergic dermatitis. Formulated to be a topical anesthetic with antiseptic and anti-inflammatory properties, EquiShield® IBH Spray soothes and treats the horse while naturally repelling insects. For use on horses.

Warnings:

For external use only.
Avoid contact with eyes and mucous membranes.

Keep out of reach of children.
Consult your veterinarian before use.

Directions:

Apply directly to affected areas as directed by your veterinarian.

Other Information:

• Store at room temperature 15˚ - 30˚C (58˚ - 86˚F).
• Store in a cool, dry place.

NDC 51031-018-06

Made in U.S.A.

#9009-03-00

KINETIC™

P.O. Box 12388, Lexington, KY 40583

877.786.9882 • Fax: 859.258.9177

www.KineticVet.com

KINETIC™VET

EquiShield® IBH SPRAY

Insect Bite Hypersensitivity

FOR VETERINARY USE ONLY

KEEP OUT OF THE REACH OF CHILDREN

Net Contents: 16 fl oz (473 ml)